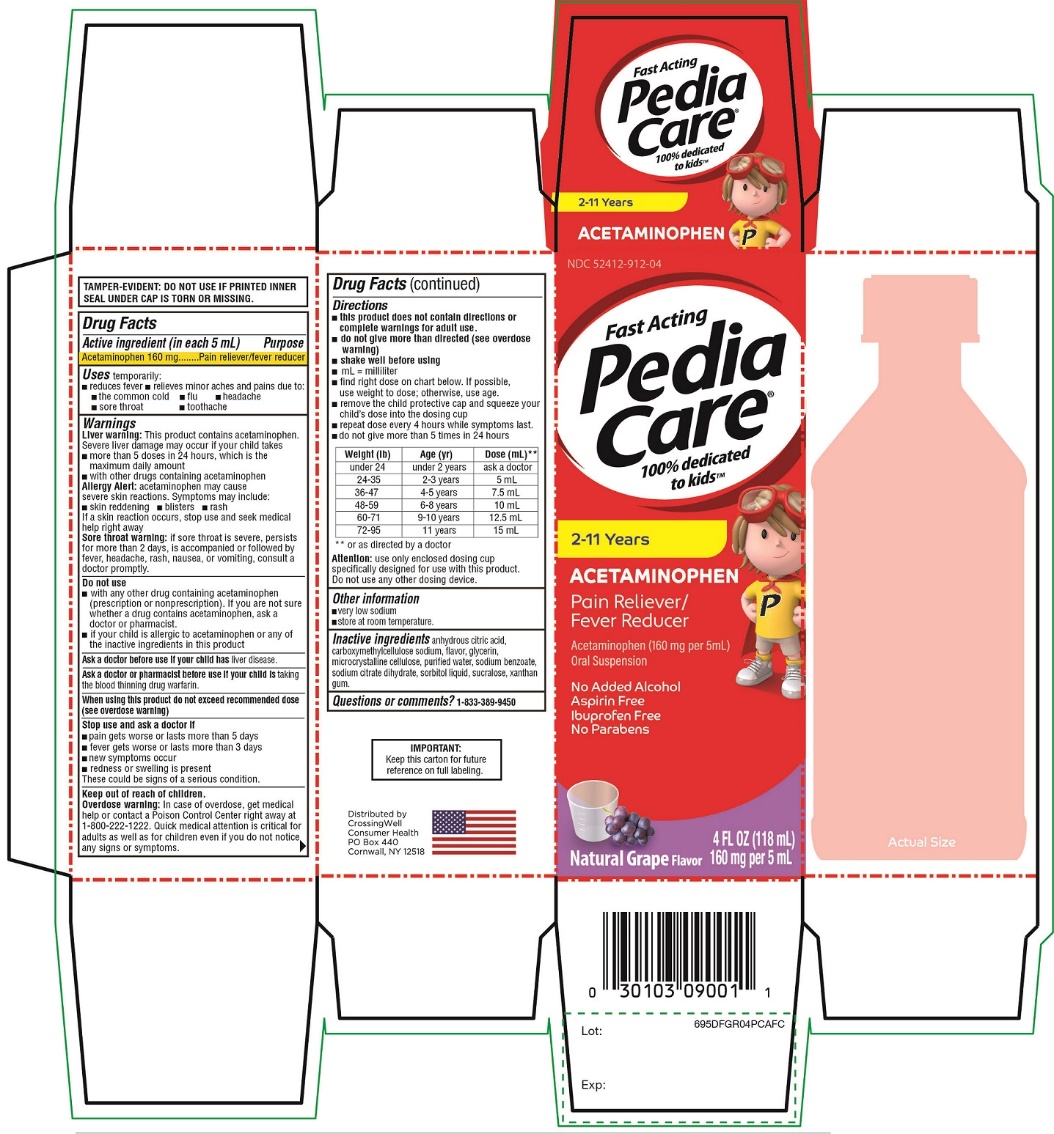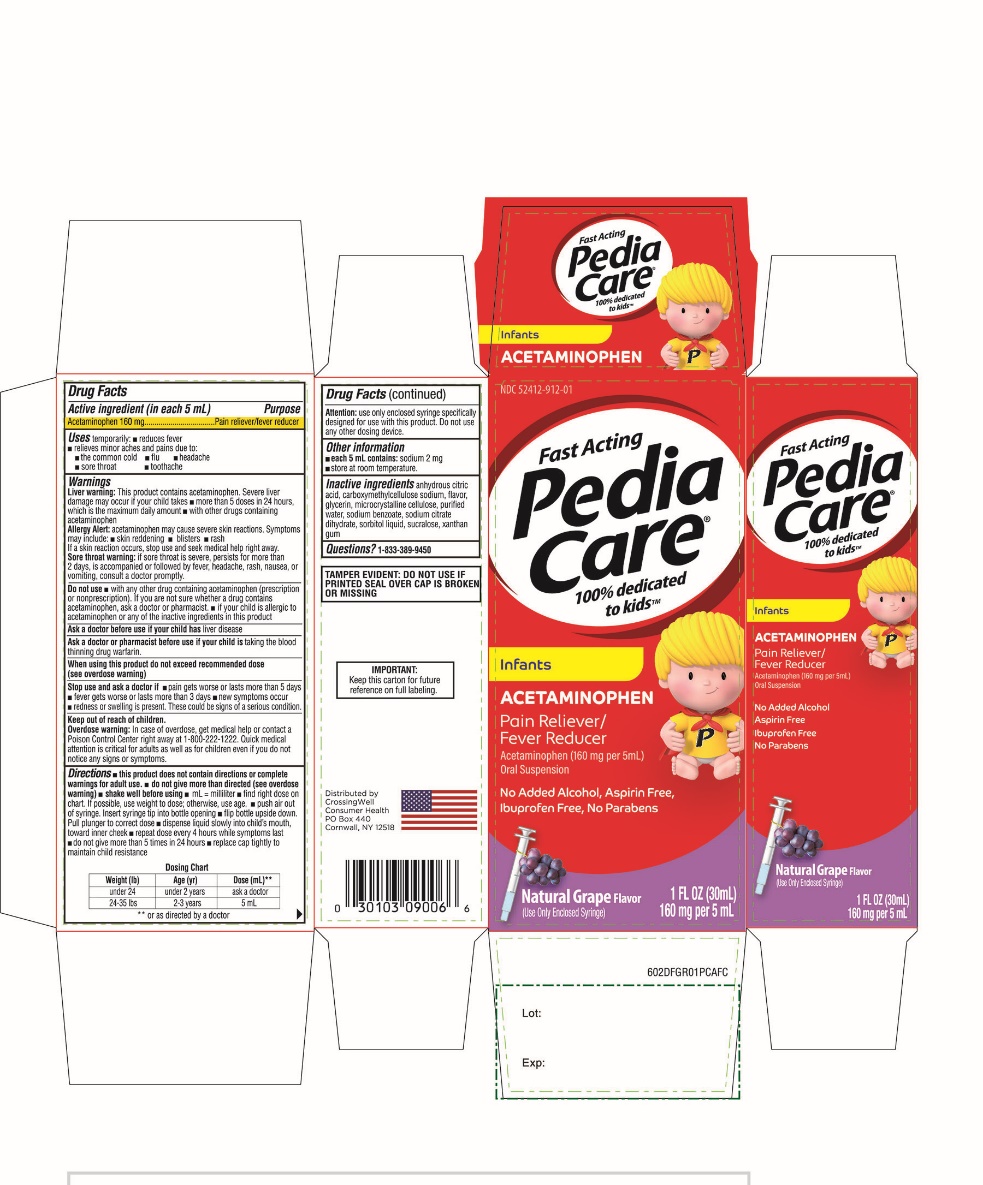 DRUG LABEL: Fast Acting

NDC: 52412-912 | Form: SUSPENSION
Manufacturer: Randob Labs., Ltd.
Category: otc | Type: HUMAN OTC DRUG LABEL
Date: 20250813

ACTIVE INGREDIENTS: ACETAMINOPHEN 160 mg/5 mL
INACTIVE INGREDIENTS: ANHYDROUS CITRIC ACID; CARBOXYMETHYLCELLULOSE SODIUM, UNSPECIFIED; GLYCERIN; MICROCRYSTALLINE CELLULOSE; WATER; SODIUM BENZOATE; SODIUM CITRATE, UNSPECIFIED FORM; SORBITOL SOLUTION; SUCRALOSE; XANTHAN GUM

Crossing well Health Pedia Care Pain + Fever Drug Facts

Drug Facts

Active ingredient (in each 5 mL)

Acetaminophen 160 mg

Purpose

Pain reliever/fever reducer

Uses

temporarily:

- reduces fever
- relieves minor aches and pains due to:
  - the common cold
  - flu
  - headache
  - sore throat
  - toothache

Warnings

Liver warning

This product contains acetaminophen. Severe liver damage may occur if your child takes

- more than 5 doses in 24 hours, which is the maximum daily amount
- with other drugs containing acetaminophen

Allergy alert:acetaminophen may cause severe skin reactions.

Symptoms may include:

- skin reddening
- blisters
- rash

If a skin reaction occurs, stop use and seek medical help right away.

Sore throat warning:if sore throat is severe, persists for more than 2 days, is accompanied or followed by fever, headache, rash, nausea, or vomiting, consult a doctor promptly.

Do not use

- with any other drug containing acetaminophen (prescription or nonprescription). If you are not sure whether a drug contains acetaminophen, ask a doctor or pharmacist.
- if your child is allergic to acetaminophen or any of the inactive ingredients in this product

Ask a doctor before use if your child hasliver disease

Ask a doctor or pharmacist before use if your child istaking the blood thinning drug warfarin

When using this product do not exceed recommended dose (see overdose warning)

Stop use and ask a doctor if

- pain gets worse or lasts more than 5 days
- fever gets worse or lasts more than 3 days
- new symptoms occur
- redness or swelling is present

These could be signs of a serious condition.

Keep out of reach of children.

Overdose warning

In case of overdose, get medical help or contact a Poison Control Center right away. (1-800-222-1222) Quick medical attention is critical for adults as well as for children even if you do not notice any signs or symptoms.

Directions

- this product does not contain directions or complete warnings for adult use.
- do not give more than directed (see overdose warning)
- shake well before using
- mL = milliliter
- find right dose on chart. If possible, use weight to dose; otherwise, use age.
- remove the child protective cap and squeeze your child’s dose into the dosing cup
- do not give more than 5 times in 24 hours

Weight (lb) | Age (yr) | Dose (mL) **
Under 24 | Under 2 years | Ask a doctor
24 – 35 | 2 – 3 years | 5 mL
36 – 47 | 4 – 5 years | 7.5 mL
48 – 59 | 6 – 8 years | 10 mL
60 – 71 | 9 – 10 years | 12.5 mL
72 – 95 | 11 years | 15 mL

**or as directed by a doctor

Attention:use only enclosed dosing cupl specifically designed for use with this product.

Do not use any other dosing device.

Other information

- very low sodium
- store at room temperature

Inactive ingredients

anhydrous citric acid, carboxymethylcellulose sodium, flavors, glycerin, microcrystalline cellulose, sodium benzoate, purified water, sodium citrate dihydrate, sorbitol liquid, sucralose, xanthan gum

Questions?

1-866-467-2748

PRINCIPAL DISPLAY PANEL

NDC 52412-912-01

Fast Acting

Pedia Care®

100% dedicated to kids™

Infants

ACETAMINOPHEN

Pain Reliever / Fever Reducer

Acetaminophen (160mg per 5 mL)

Oral Suspension

- No Added Alcohol
- Ibuprofen Free
- Aspirin Free
- No Parabens

Natural Grape Flavor

(Use only Enclosed Syringe)

1FL OZ (30mL)
160 mg per 5 mL

TAMPER EVIDENT: DO NOT USE IF PRINTED SEAL OVER CAP IS BROKEN OR MISSING

IMPORTANT: Keep this carton for future reference on full labeling.

Package Label of 1 FLOZ (30 mL)